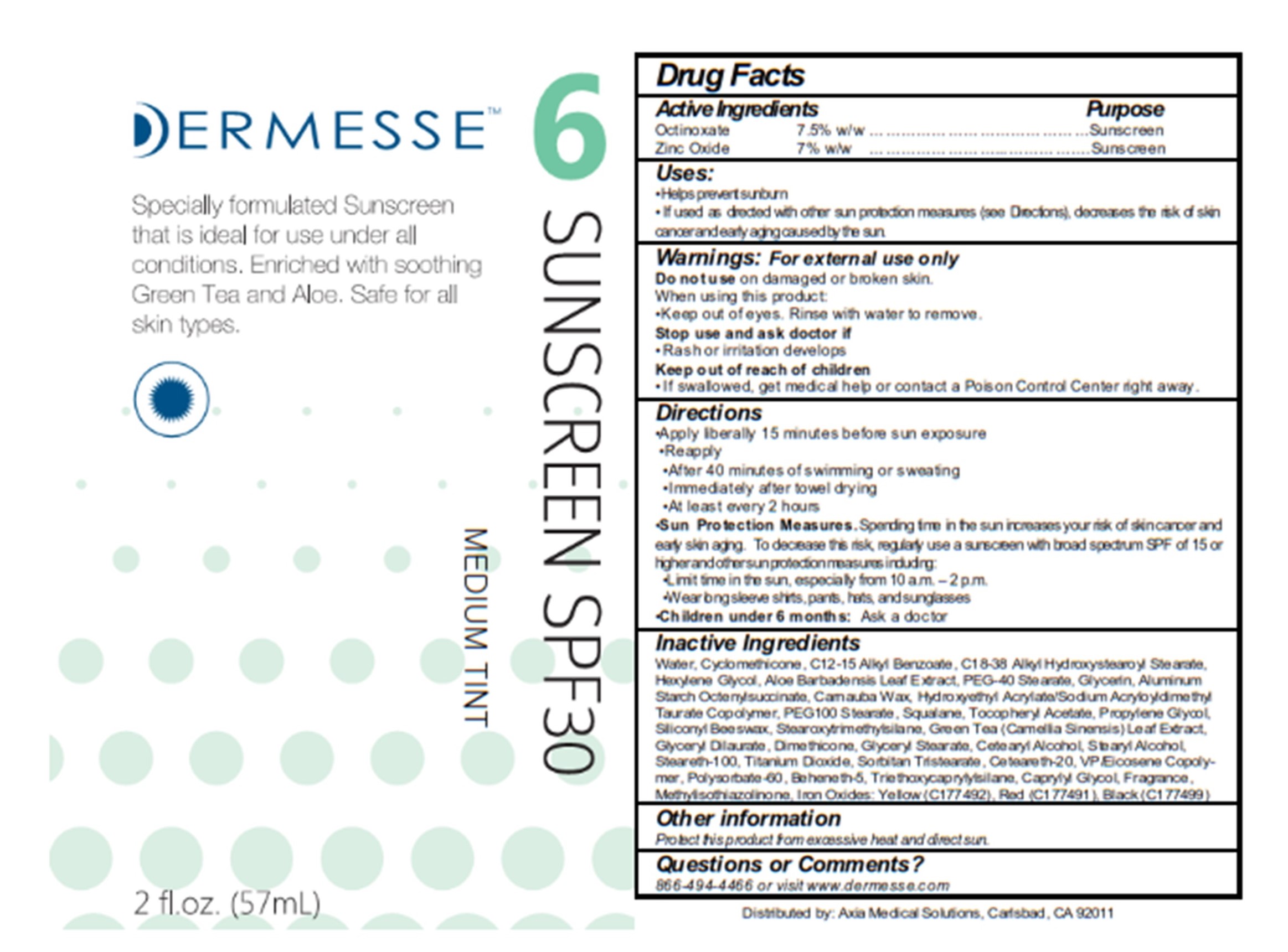 DRUG LABEL: Dermesse Sunscreen SPF30 Medium Tint
NDC: 68723-331 | Form: LOTION
Manufacturer: Axia Medical Solutions, LLC
Category: otc | Type: HUMAN OTC DRUG LABEL
Date: 20210712

ACTIVE INGREDIENTS: OCTINOXATE 75 mg/1 g; ZINC OXIDE 70 mg/1 g
INACTIVE INGREDIENTS: WATER; CYCLOMETHICONE; ALKYL (C12-15) BENZOATE; HEXYLENE GLYCOL; ALOE VERA LEAF; PEG-40 STEARATE; GLYCERIN; ALUMINUM STARCH OCTENYLSUCCINATE; CARNAUBA WAX; HYDROXYETHYL ACRYLATE/SODIUM ACRYLOYLDIMETHYL TAURATE COPOLYMER (100000 MPA.S AT 1.5%); PEG-100 STEARATE; SQUALANE; .ALPHA.-TOCOPHEROL ACETATE; PROPYLENE GLYCOL; BIS-PEG-12 DIMETHICONE (500 MPA.S); STEAROXYTRIMETHYLSILANE; GREEN TEA LEAF; GLYCERYL DILAURATE; DIMETHICONE 350; GLYCERYL STEARATE SE; CETEARYL STEARATE; STEARYL ALCOHOL; STEARETH-100; TITANIUM DIOXIDE; SORBITAN TRISTEARATE; POLYOXYL 20 CETOSTEARYL ETHER; VINYLPYRROLIDONE/EICOSENE COPOLYMER; POLYSORBATE 60; BEHENETH-5; TRIETHOXYCAPRYLYLSILANE; CAPRYLYL GLYCOL; METHYLISOTHIAZOLINONE; FERRIC OXIDE YELLOW; FERRIC OXIDE RED; FERROSOFERRIC OXIDE

Dermessse Sunscreen SPF30 Tint

Active Ingredients

Octinoxiate 7.5% w/w

Zinc Oxide 7% w/w

Purpose

Sunscreen

Uses:

• Helps prevent sunburn

• If used as directed with other sun protection measures (see Directions), decreases the risk of skin cancer and early aging caused by the sun.

Warnings:

For external use only

Do not use on damaged or broken skin.

When using this product:

• Keep out of eyes. Rinse with water to remove.

Stop use and ask doctor if

• Rash or irritation develops

Keep out of reach of children

• If swallowed, get medical help or contact a Poison Control Center right away.

Directions

• Apply liberally 15 minutes before sun exposure

• Reapply

• After 40 minutes of swimming or sweating

• Immediately after towel drying

• At least every 2 hours

• Sun Protection Measures. Spending time in the sun increases your risk of skin cancer and early skin aging. To decrease this risk, regularly use a sunscreen with broad spectrum SPF of 15 or higher and other sun protection measures including:

• Limit time in the sun, especially from 10 a.m. - 2 p.m.

• Wear long sleeve shirts, pants, hats, and sunglasses

Children under 6 months: Ask a doctor

Inactive Ingredients

Water, Cyclomethicone, C12-15 Alkyl Benzoate, C18-38 Alkyl Hydroxystearoyl Stearate, Hexylene Glycol, Aloe Barbadensis Leaf Extract, PEG-40 Stearate, Glycerin, Aluminum Starch Octenylsuccinate, Carnauba Wax, Hydroxyethyl Acrylate/Sodium Acryloyldimethyl Taurate Copolymer, PEG100 Stearate, Squalane, Tocopheryl Acetate, Propylene Glycol, Siliconyl Beeswax, Stearoxytrimethylsilane, Green Tea (Camellia Sinensis) Leaf Extract, Glyceryl Dilaurate, Dimethicone, Glyceryl Stearate, Cetearyl Alcohol, Stearyl Alcohol, Steareth-100, Titanium Dioxide, Sorbitan Tristearate, Ceteareth-20, VP/Eicosene Copolymer, Polysorbate-60, Beheneth-5, Triethoxycaprylylsilane, Caprylyl Glycol, Fragrance, Methylisothiazolinone, Iron Oxides: Yellow (C177492), Red (C177491), Black (C177499)

Other information

Protect this product from excessive heat and direct sun.

Questions or Comments?

866-494-4466 or visit www.dermesse.com